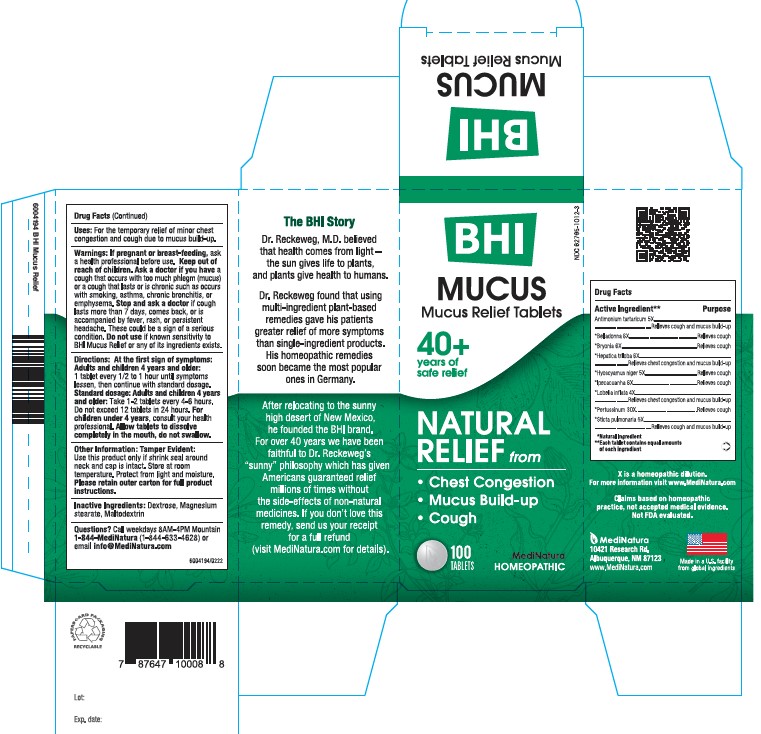 DRUG LABEL: Mucus Relief
NDC: 62795-1012 | Form: TABLET
Manufacturer: MediNatura Inc
Category: homeopathic | Type: HUMAN OTC DRUG LABEL
Date: 20221214

ACTIVE INGREDIENTS: ANTIMONY POTASSIUM TARTRATE 5 [hp_X]/1 1; ATROPA BELLADONNA 6 [hp_X]/1 1; BRYONIA ALBA WHOLE 6 [hp_X]/1 1; ANEMONE HEPATICA VAR. OBTUSA 6 [hp_X]/1 1; HYOSCYAMUS NIGER 5 [hp_X]/1 1; IPECAC 6 [hp_X]/1 1; LOBELIA INFLATA 4 [hp_X]/1 1; HUMAN SPUTUM, BORDETELLA PERTUSSIS INFECTED 30 [hp_X]/1 1; LOBARIA PULMONARIA 5 [hp_X]/1 1
INACTIVE INGREDIENTS: MAGNESIUM STEARATE; MALTODEXTRIN; DEXTROSE

BHI Mucus Tablet

ACTIVE INGREDIENT

Each tablet contains:

Antimonium tartaricum 5X, *Belladonna 6X, *Bryonia alba 6X, *Hepatica triloba 6X, *Hyoscyamus niger 5X, *Ipecacuanha 6X, *Lobelia inflata 4X, *Pertussinum 30X, *Sticta pulmonaria 5X 33.3 mg each.

*Natural Ingredients

INACTIVE INGREDIENT

Inactive Ingredients: Dextrose, Magnesium Stearate, Maltodextrin

PURPOSE

Mucus Relief Tablets

Relieves:

• Chest Congestion

• Mucus Build-up

• Cough

Uses:

For the temporary relief of minor chest congestion and cough due to mucus build-up

DIRECTIONS

At first sign of symptoms:

Adults and children 4 years and older: 1 tablet every 1/2 to 1 hour until symptoms lessen, then continue with standard dosage.

Standard dosage: Adults and children 4 years and older: Take 1-2 tablets every 4 to 6 hours. Do not exceed 12 tablets in 24 hours.

For children under 4, consult your health professional.

Allow tablets to dissolve completely in the mouth, do not swallow.

KEEP OUT OF REACH OF CHILDREN

PACKAGE LABEL

Add image transcription here...